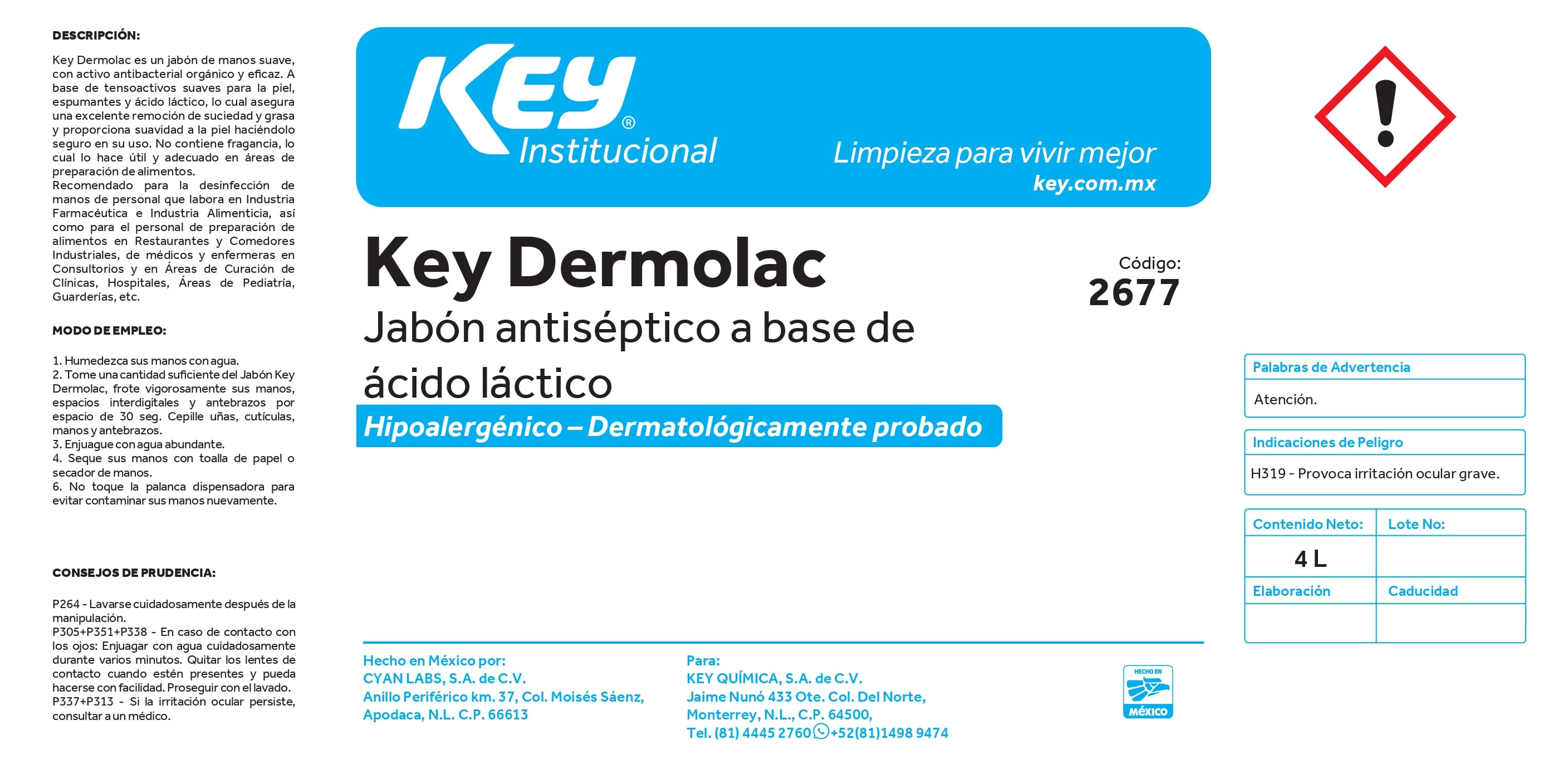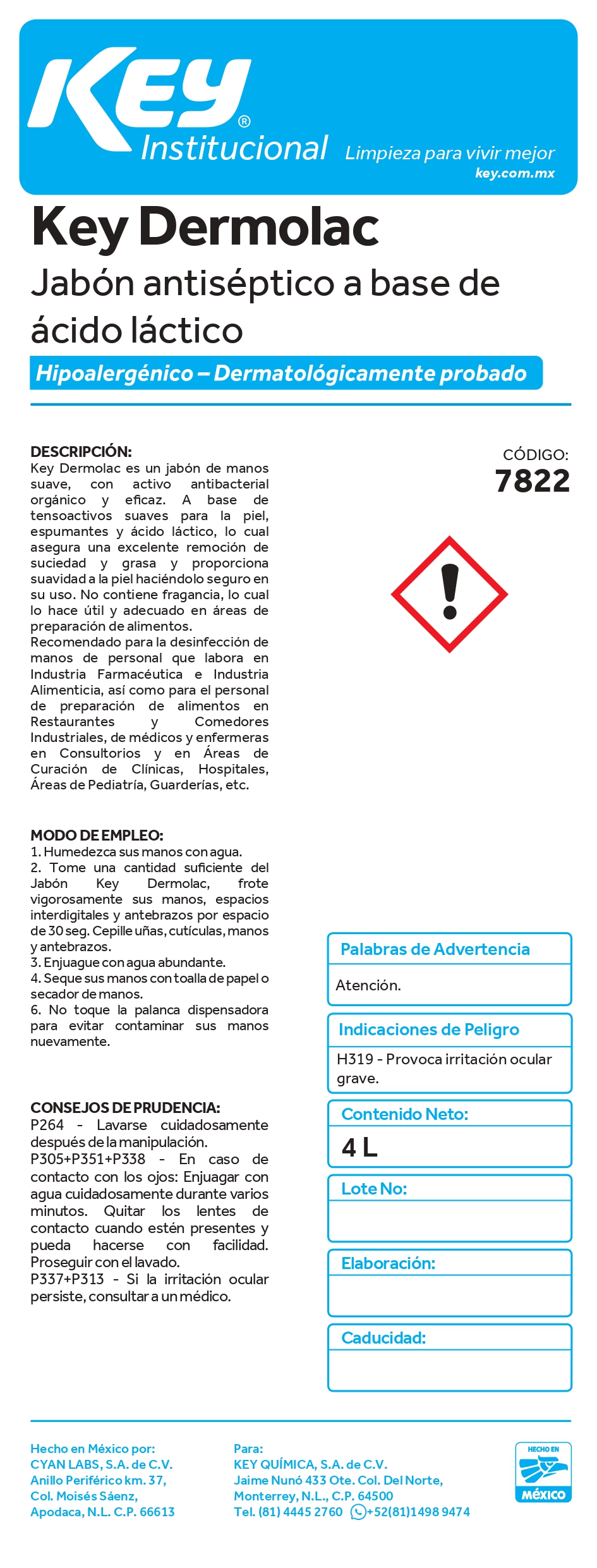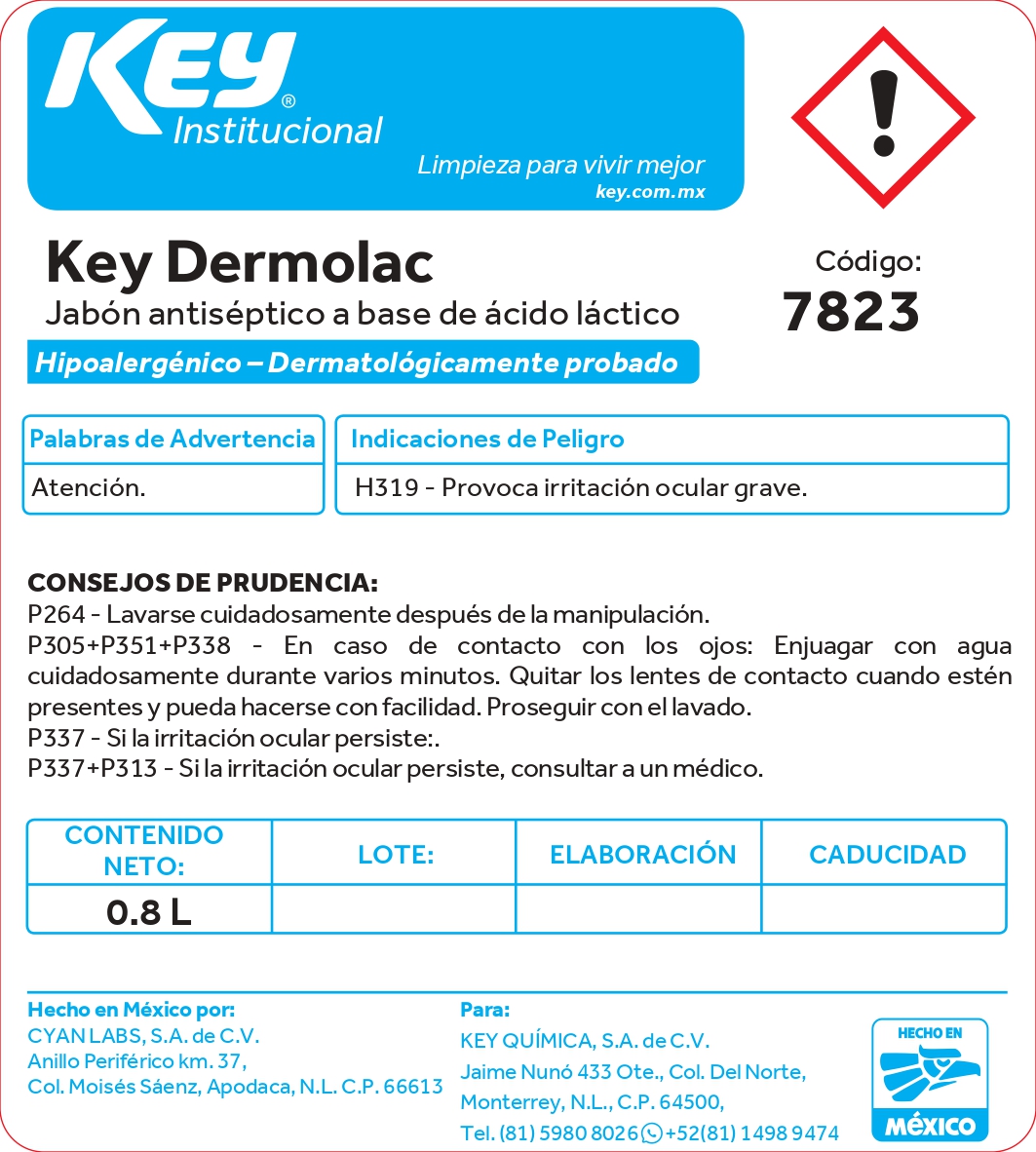 DRUG LABEL: Key Dermolac
NDC: 58345-105 | Form: LIQUID
Manufacturer: Key Química S.A. de C.V.
Category: otc | Type: HUMAN OTC DRUG LABEL
Date: 20250107

ACTIVE INGREDIENTS: LACTIC ACID, L- 1.6 g/100 mL
INACTIVE INGREDIENTS: WATER; SODIUM LAURETH SULFATE; DIRECT RED 81; SODIUM HYDROXIDE; COCAMIDOPROPYL BETAINE; SODIUM CHLORIDE; EDETATE SODIUM; CARMOISINE

58345-105

Active ingredients

- L-(+)-lactic acid 1.6 %

Purpose

Antiseptic

Do not use this product in or near the eyes.

Stop use if irritation or redness develop. If conditions persist for more than 72 hours, consult a doctor.

Keep out of reach of children. If swallowed, seek inmediate medical attention or call a poison center.

Inactive ingredients

- Water

- Sodium Laureth Sulfate

- Sodium chloride

- Cocamidopropyl betaine

- Sodium hydroxide

- Tetrasodium EDTA

- Acid Red 14

- Direct Red 81

Directions

Wet hands thoroughly with product ant rise at the end.

Use

To decrease bacteria on skin that could cause diseases.

Warnings

- For external use only.